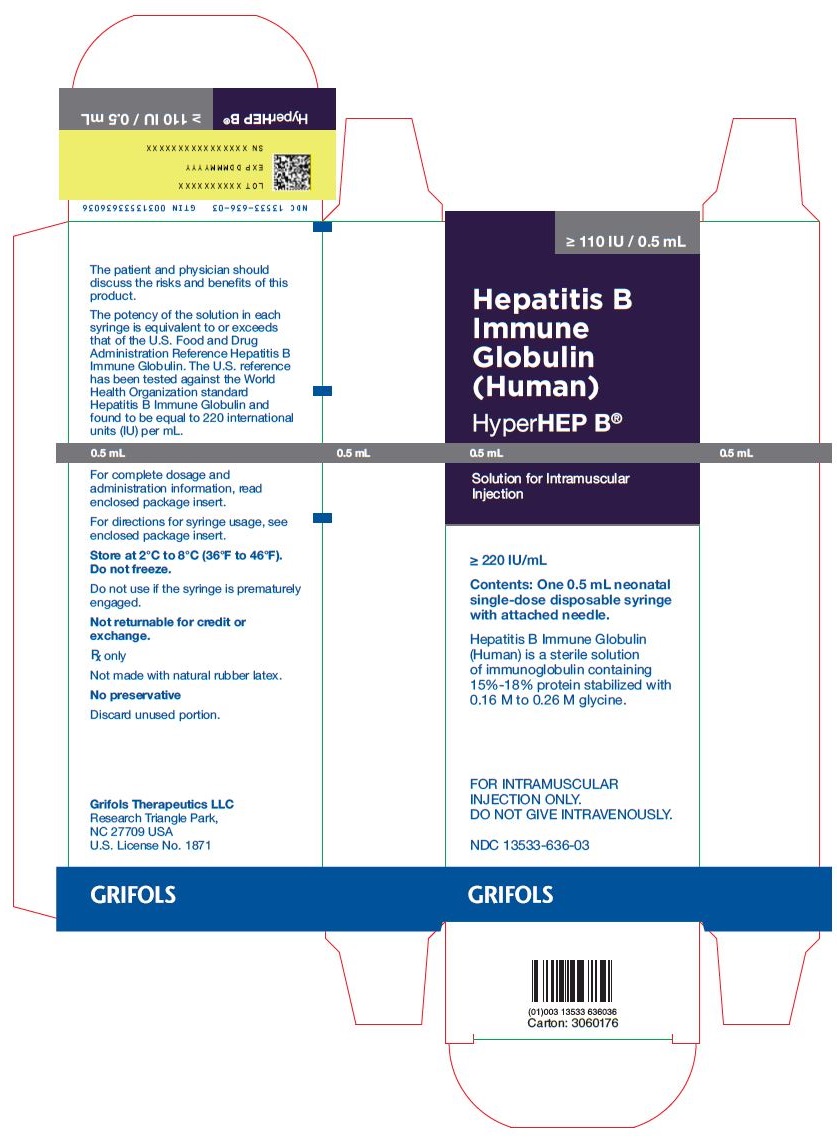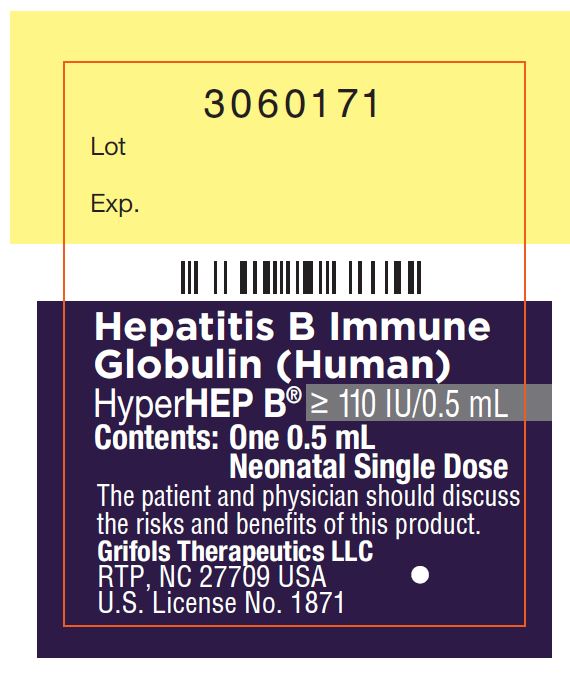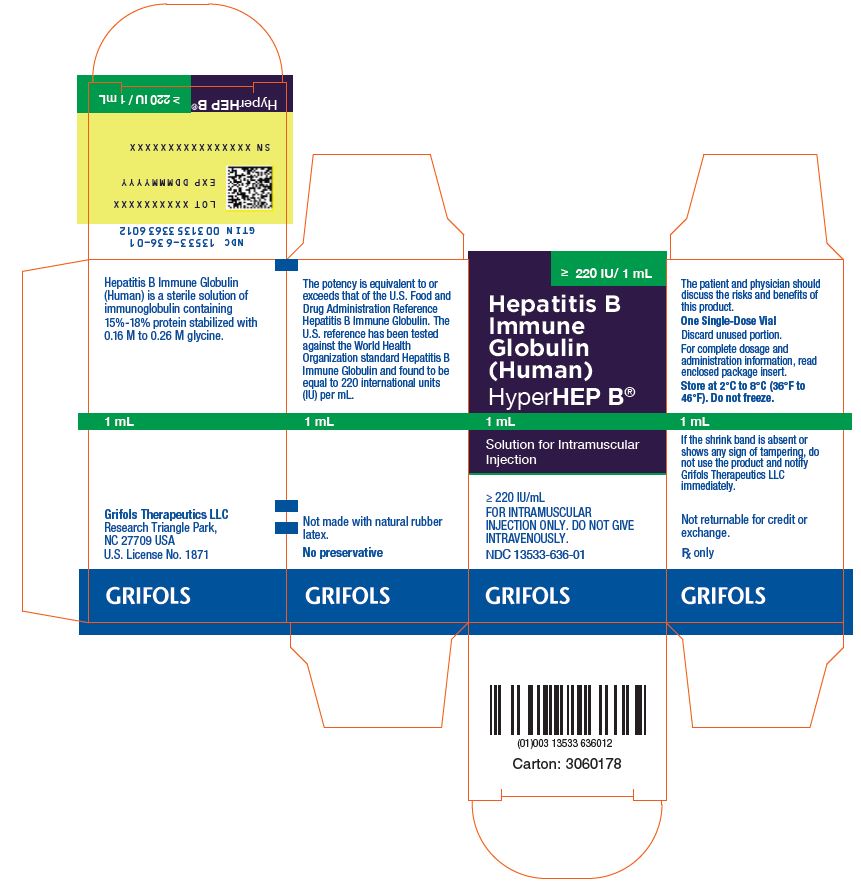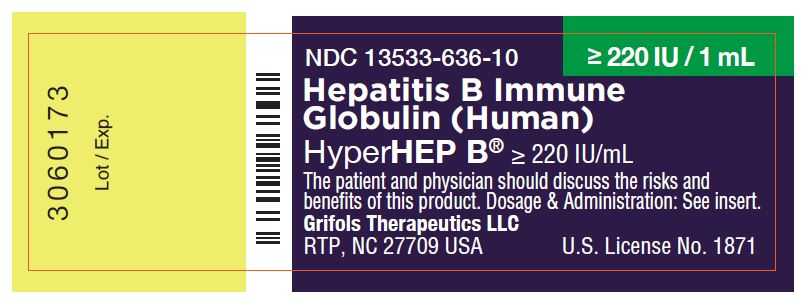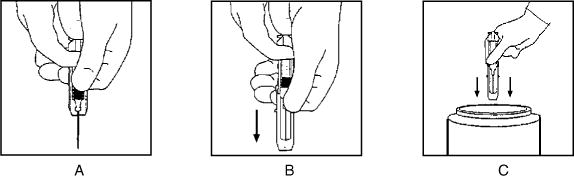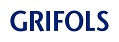 DRUG LABEL: HYPERHEP B
NDC: 13533-636 | Form: INJECTION
Manufacturer: GRIFOLS USA, LLC
Category: other | Type: PLASMA DERIVATIVE
Date: 20240920

ACTIVE INGREDIENTS: Human Hepatitis B Virus Immune Globulin 220 [iU]/1 mL
INACTIVE INGREDIENTS: Glycine; Water

Hepatitis B Immune Globulin
(Human)
HyperHEP B®

DESCRIPTION

Hepatitis B Immune Globulin (Human) — HyperHEP B® is a clear or slightly opalescent, and colorless or pale yellow sterile solution of human hepatitis B immune globulin for intramuscular administration. HyperHEP B contains no preservative. HyperHEP B is prepared from pools of human plasma collected from healthy donors by a combination of cold ethanol fractionation, caprylate precipitation and filtration, caprylate incubation, anion exchange chromatography, nanofiltration and low pH incubation. HyperHEP B consists of a 15% to 18% protein solution at a pH of 4.1 to 4.8 in 0.16 M to 0.26 M glycine. The product contains anti-HBs antibody equivalent to or exceeding the potency of anti-HBs in a U.S. reference hepatitis B immune globulin (Center for Biologics Evaluation and Research, FDA). The U.S. reference has been tested against the World Health Organization standard Hepatitis B Immune Globulin and found to be equal to 220 international units (IU) per mL.

When medicinal biological products are administered, the risk of infectious diseases due to transmission of pathogens cannot be totally excluded. However, in the case of products prepared from human plasma, the risk of transmission of pathogens is reduced by epidemiological surveillance of the donor population and selection of individual donors by medical interview; testing of individual donations and plasma pools; and the presence in the manufacturing processes of steps with demonstrated capacity to inactivate/remove pathogen.

In the manufacturing process of HyperHEP B, there are several steps with the capacity for viral inactivation or removal.(1) The main steps of the manufacturing process that contribute to the virus clearance capacity are as follows:

- Caprylate precipitation/depth filtration
- Caprylate incubation
- Depth filtration
- Column chromatography
- Nanofiltration
- Low pH final container incubation

To provide additional assurance of the pathogen safety of the final product, the capacity of the HyperHEP B manufacturing process to remove and/or inactivate viruses has been demonstrated by laboratory spiking studies on a scaled down process model using a wide range of viruses with diverse physicochemical properties.

The combination of all of the above mentioned measures provides the final product with a high margin of safety from the potential risk of transmission of infectious viruses.

The caprylate/chromatography manufacturing process was also investigated for its capacity to decrease the infectivity of an experimental agent of transmissible spongiform encephalopathy (TSE), considered as a model for the variant Creutzfeldt-Jakob disease (vCJD), and Creutzfeldt-Jakob disease (CJD) agents.(1) These studies provide reasonable assurance that low levels of vCJD/CJD agent infectivity, if present in the starting material, would be removed by the caprylate/chromatography manufacturing process.

CLINICAL PHARMACOLOGY

Hepatitis B Immune Globulin (Human) provides passive immunization for individuals exposed to the hepatitis B virus (HBV) as evidenced by a reduction in the attack rate of hepatitis B following its use.(2-7) The administration of the usual recommended dose of this immune globulin generally results in a detectable level of circulating anti-HBs which persists for approximately 2 months or longer. The highest antibody (IgG) serum levels were seen in the following distribution of subjects studied: (8)

DAY | % OF SUBJECTS
3 | 38.9%
7 | 41.7%
14 | 11.1%
21 | 8.3%

Mean values for half-life were between 17.5 and 25 days, with the shortest being 5.9 days and the longest 35 days.(8)

Cases of type B hepatitis are rarely seen following exposure to HBV in persons with preexisting anti-HBs. No confirmed instance of transmission of hepatitis B has been associated with this product.

In a clinical study, 12 healthy human adults receiving another hyperimmune immune globulin product, Rabies Immune Globulin (Human), HyperRAB®, prepared by the same manufacturing process, detectable passive antibody titers were observed in the serum of all subjects by 24 hours post injection and persisted through the 21 day study period.

INDICATIONS AND USAGE

Recommendations on post-exposure prophylaxis are based on available efficacy data and on the likelihood of future HBV exposure for the person requiring treatment. In all exposures, a regimen combining Hepatitis B Immune Globulin (Human) with hepatitis B vaccine will provide both short- and long-term protection, will be less costly than the two-dose Hepatitis B Immune Globulin (Human) treatment alone, and is the treatment of choice.(9)

HyperHEP B is indicated for post-exposure prophylaxis in the following situations:

Acute Exposure to Blood Containing HBsAg

After either parenteral exposure, e.g., by accidental “needlestick” or direct mucous membrane contact (accidental splash), or oral ingestion (pipetting accident) involving HBsAg-positive materials such as blood, plasma or serum. For inadvertent percutaneous exposure, a regimen of two doses of Hepatitis B Immune Globulin (Human), one given after exposure and one a month later, is about 75% effective in preventing hepatitis B in this setting.

Perinatal Exposure of Infants Born to HBsAg-positive Mothers

Infants born to HBsAg-positive mothers are at risk of being infected with hepatitis B virus and becoming chronic carriers.(6,9-11) This risk is especially great if the mother is HBeAg-positive.(13-15) For an infant with perinatal exposure to an HBsAg-positive and HBeAg-positive mother, a regimen combining one dose of Hepatitis B Immune Globulin (Human) at birth with the hepatitis B vaccine series started soon after birth is 85%–95% effective in preventing development of the HBV carrier state.(9,15) Regimens involving either multiple doses of Hepatitis B Immune Globulin (Human) alone or the vaccine series alone have 70%–90% efficacy, while a single dose of Hepatitis B Immune Globulin (Human) alone has only 50% efficacy.(9,16)

Sexual Exposure to an HBsAg-positive Person

Sex partners of HBsAg-positive persons are at increased risk of acquiring HBV infection. For sexual exposure to a person with acute hepatitis B, a single dose of Hepatitis B Immune Globulin (Human) is 75% effective if administered within 2 weeks of last sexual exposure.(9)

Household Exposure to Persons with Acute HBV Infection

Since infants have close contact with primary care-givers and they have a higher risk of becoming HBV carriers after acute HBV infection, prophylaxis of an infant less than 12 months of age with Hepatitis B Immune Globulin (Human) and hepatitis B vaccine is indicated if the mother or primary care-giver has acute HBV infection.(9)

Administration of Hepatitis B Immune Globulin (Human) either preceding or concomitant with the commencement of active immunization with Hepatitis B Vaccine provides for more rapid achievement of protective levels of hepatitis B antibody, than when the vaccine alone is administered.(17) Rapid achievement of protective levels of antibody to hepatitis B virus may be desirable in certain clinical situations, as in cases of accidental inoculations with contaminated medical instruments.(17) Administration of Hepatitis B Immune Globulin (Human) either 1 month preceding or at the time of commencement of a program of active vaccination with Hepatitis B Vaccine has been shown not to interfere with the active immune response to the vaccine.(17)

CONTRAINDICATIONS

None known.

WARNINGS

HyperHEP B is made from human plasma. Products made from human plasma may contain infectious agents, such as viruses, and, theoretically, the Creutzfeldt-Jakob Disease (CJD) agent that can cause disease. The risk that such products will transmit an infectious agent has been reduced by screening plasma donors for prior exposure to certain viruses, by testing for the presence of certain current virus infections, and by inactivating and/or removing certain viruses. Despite these measures, such products can still potentially transmit disease. There is also the possibility that unknown infectious agents may be present in such products. Individuals who receive infusions of blood or plasma products may develop signs and/or symptoms of some viral infections, particularly hepatitis C. ALL infections thought by a physician possibly to have been transmitted by this product should be reported by the physician or other healthcare provider to Grifols Therapeutics LLC [1-800-520-2807].

The physician should discuss the risks and benefits of this product with the patient, before prescribing or administering it to the patient.

HyperHEP B should be given with caution to patients with a history of prior systemic allergic reactions following the administration of human immune globulin preparations. Epinephrine should be available.

In patients who have severe thrombocytopenia or any coagulation disorder that would contraindicate intramuscular injections, Hepatitis B Immune Globulin (Human) should be given only if the expected benefits outweigh the risks.

PRECAUTIONS

General

HyperHEP B should not be administered intravenously because of the potential for serious reactions. Injections should be made intramuscularly, and care should be taken to draw back on the plunger of the syringe before injection in order to be certain that the needle is not in a blood vessel. Intramuscular injections are preferably administered in the deltoid muscle of the upper arm or lateral thigh muscle. The gluteal region should not be used as an injection site because of the risk of injury to the sciatic nerve.(18) An individual decision as to which muscle is injected must be made for each patient based on the volume of material to be administered.

Laboratory Tests

None required.

Drug Interactions

Although administration of Hepatitis B Immune Globulin (Human) did not interfere with measles vaccination,(19) it is not known whether Hepatitis B Immune Globulin (Human) may interfere with other live virus vaccines. Therefore, use of such vaccines should be deferred until approximately 3 months after Hepatitis B Immune Globulin (Human) administration. Hepatitis B Vaccine may be administered at the same time, but at a different injection site, without interfering with the immune response.(17) No interactions with other products are known.

Pregnancy

Animal reproduction studies have not been conducted with HyperHEP B. It is also not known whether HyperHEP B can cause fetal harm when administered to a pregnant woman or can affect reproduction capacity. HyperHEP B should be given to a pregnant woman only if clearly needed.

Pediatric Use

Safety and effectiveness in the pediatric population have not been established.

ADVERSE REACTIONS

Local pain and tenderness at the injection site, urticaria and angioedema may occur; anaphylactic reactions, although rare, have been reported following the injection of human immune globulin preparations.(20)

OVERDOSAGE

Although no data are available, clinical experience with other immunoglobulin preparations suggests that the only manifestations would be pain and tenderness at the injection site.

DOSAGE AND ADMINISTRATION

Acute Exposure to Blood Containing HBsAg(16)

Table 1 summarizes prophylaxis for percutaneous (needlestick or bite), ocular, or mucous-membrane exposure to blood according to the source of exposure and vaccination status of the exposed person. For greatest effectiveness, passive prophylaxis with Hepatitis B Immune Globulin (Human) should be given as soon as possible after exposure (its value beyond 7 days of exposure is unclear). If Hepatitis B Immune Globulin (Human) is indicated (see Table 1), an injection of 0.06 mL/kg of body weight should be administered intramuscularly (see PRECAUTIONS) as soon as possible after exposure and within 24 hours, if possible. Consult Hepatitis B Vaccine package insert for dosage information regarding that product.

Table 1. (adapted from (21))
Recommendations for Hepatitis B Prophylaxis Following Percutaneous or Permucosal Exposure
 | Exposed Person
Source | Unvaccinated | Vaccinated
HBsAg-Positive | 1. Hepatitis B Immune Globulin (Human) x1 immediately [Hepatitis B Immune Globulin (Human), dose 0.06 mL / kg IM.] | 1. Test exposed person for anti-HBs.
HBsAg-Positive | 2. Initiate HB Vaccine Series [HB Vaccine dose 20 μg IM for adults; 10 μg IM for infants or children under 10 years of age. First dose within 1 week; second and third doses, 1 and 6 months later.] | 2. If inadequate antibody, [Less than 10 sample ratio units (SRU) by radioimmunoassay (RIA), negative by enzyme immunoassay (EIA).] Hepatitis B Immune Globulin (Human) (x1) immediately plus HB Vaccine booster dose, or 2 doses of HBIG, one as soon as possible after exposure and the second 1 month later.
Known Source (High Risk) | 1. Initiate HB Vaccine Series | 1. Test Source for HBsAg only if exposed is vaccine nonresponder; if source is HBsAg-positive, give Hepatitis B Immune Globulin (Human) x1 immediately plus HB Vaccine booster dose, or 2 doses of HBIG, one as soon as possible after exposure and the second 1 month later.
Known Source (High Risk) | 2. Test source for HBsAg. If positive, Hepatitis B Immune Globulin (Human) x1 | 1. Test Source for HBsAg only if exposed is vaccine nonresponder; if source is HBsAg-positive, give Hepatitis B Immune Globulin (Human) x1 immediately plus HB Vaccine booster dose, or 2 doses of HBIG, one as soon as possible after exposure and the second 1 month later.
Low Risk HBsAg-Positive | Initiate HB Vaccine series | Nothing required.
Unknown Source | Initiate HB Vaccine series within 7 days of exposure | Nothing required.

For persons who refuse Hepatitis B Vaccine, a second dose of Hepatitis B Immune Globulin (Human) should be given 1 month after the first dose.

Prophylaxis of Infants Born to HBsAg and HBeAg Positive Mothers

Efficacy of prophylactic Hepatitis B Immune Globulin (Human) in infants at risk depends on administering Hepatitis B Immune Globulin (Human) on the day of birth. It is therefore vital that HBsAg-positive mothers be identified before delivery.

Hepatitis B Immune Globulin (Human) (0.5 mL) should be administered intramuscularly (IM) to the newborn infant after physiologic stabilization of the infant and preferably within 12 hours of birth. Hepatitis B Immune Globulin (Human) efficacy decreases markedly if treatment is delayed beyond 48 hours. Hepatitis B Vaccine should be administered IM in three doses of 0.5 mL of vaccine (10 μg) each. The first dose should be given within 7 days of birth and may be given concurrently with Hepatitis B Immune Globulin (Human) but at a separate site. The second and third doses of vaccine should be given 1 month and 6 months, respectively, after the first. If administration of the first dose of Hepatitis B Vaccine is delayed for as long as 3 months, then a 0.5 mL dose of Hepatitis B Immune Globulin (Human) should be repeated at 3 months. If Hepatitis B Vaccine is refused, the 0.5 mL dose of Hepatitis B Immune Globulin (Human) should be repeated at 3 and 6 months. Hepatitis B Immune Globulin (Human) administered at birth should not interfere with oral polio and diphtheria-tetanus-pertussis vaccines administered at 2 months of age.(16)

Sexual Exposure to an HBsAg-positive Person

All susceptible persons whose sex partners have acute hepatitis B infection should receive a single dose of HBIG (0.06 mL/kg) and should begin the hepatitis B vaccine series if prophylaxis can be started within 14 days of the last sexual contact or if sexual contact with the infected person will continue (see Table 2 below). Administering the vaccine with HBIG may improve the efficacy of postexposure treatment. The vaccine has the added advantage of conferring long-lasting protection.(9)

Table 2. (adapted from (22))
Recommendations for Postexposure Prophylaxis for Sexual Exposure to Hepatitis B
HBIG [HBIG = Hepatitis B Immune Globulin (Human)] |  | Vaccine
Dose | Recommended timing | Dose | Recommended timing
0.06 mL/kg IM [IM = intramuscularly] | Single dose within 14 days of last sexual contact | 1.0 mL IM | First dose at time of HBIG treatment [The first dose can be administered the same time as the HBIG dose but at a different site; subsequent doses should be administered as recommended for specific vaccine.]

Household Exposure to Persons with Acute HBV Infection

Prophylactic treatment with a 0.5 mL dose of Hepatitis B Immune Globulin (Human) and hepatitis B vaccine is indicated for infants <12 months of age who have been exposed to a primary care-giver who has acute hepatitis B. Prophylaxis for other household contacts of persons with acute HBV infection is not indicated unless they have had identifiable blood exposure to the index patient, such as by sharing toothbrushes or razors. Such exposures should be treated like sexual exposures. If the index patient becomes an HBV carrier, all household contacts should receive hepatitis B vaccine. (9)

Hepatitis B Immune Globulin (Human) may be administered at the same time (but at a different site), or up to 1 month preceding Hepatitis B Vaccination without impairing the active immune response from Hepatitis B Vaccination.(17)

Parenteral drug products should be inspected visually for particulate matter and discoloration prior to administration, whenever solution and container permit.

Administer intramuscularly. Do not inject intravenously.

Hepatitis B Immune Globulin (Human) — HyperHEP B® is supplied in a syringe with an attached UltraSafe® Needle Guard for your protection and convenience, as well as in vials. Please follow instructions below for proper use of syringe and UltraSafe® Needle Guard.

Directions for Syringe Usage

1. Remove the prefilled syringe from the package. Lift syringe by barrel,
  not by plunger.
2. Twist the plunger rod clockwise until the threads are seated.
3. With the needle shield secured on the syringe tip, push the plunger rod forward a few millimeters to break any friction seal between the stopper and the glass syringe barrel.
4. Remove the needle shield and expel air bubbles. [Do not remove the needle shield to prepare the product for administration until immediately prior to the anticipated injection time.]
5. Proceed with hypodermic needle puncture.
6. Aspirate prior to injection to confirm that the needle is not in a vein or artery.
7. Inject the medication.
8. Keeping your hands behind the needle, grasp the guard with free hand and slide forward toward needle until it is completely covered and guard clicks into place. If audible click is not heard, guard may not be completely activated. (See Diagrams A and B)
9. Place entire prefilled glass syringe with guard activated into an approved sharps container for proper disposal. (See Diagram C)

A number of factors could reduce the efficacy of this product or even result in an ill effect following its use. These include improper storage and handling of the product after it leaves our hands, diagnosis, dosage, method of administration and biological differences in individual patients. Because of these factors, it is important that this product be stored properly and that the directions be followed carefully during use.

HOW SUPPLIED

HyperHEP B is supplied in a 0.5 mL neonatal single dose syringe with attached needle, a 1 mL single dose syringe with attached needle and a 1 mL and a 5 mL single dose vial.
HyperHEP B contains no preservative and is not made with natural rubber latex.

NDC Number | Size
13533-636-03 | 0.5 mL syringe
13533-636-02 | 1 mL syringe
13533-636-01 | 1 mL vial
13533-636-05 | 5 mL vial

STORAGE

Store at 2–8°C (36–46°F). Do not freeze. Do not use after expiration date. Discard unused portion.

CAUTION

Rx only

U.S. federal law prohibits dispensing without prescription.

REFERENCES

1. Barnette D, Roth NJ, Hotta J, et al. Pathogen safety profile of a 10% IgG preparation manufactured using a depth filtration-modified process. Biologicals 2012;40:247-53.
2. Grady GF, Lee VA: Hepatitis B immune globulin — prevention of hepatitis from accidental exposure among medical personnel. N Engl J Med 293(21):1067–70, 1975.
3. Seeff LB, Zimmerman HJ, Wright EC, et al: Efficacy of hepatitis B immune serum globulin after accidental exposure. Lancet 2(7942):939-41, 1975.
4. Krugman S, Giles JP: Viral hepatitis, type B (MS-2-strain). Further observations on natural history and prevention. N Engl J Med 288(15):755-60, 1973.
5. Current trends: Health status of Indochinese refugees: malaria and hepatitis B. MMWR 28(39):463-4; 469-70, 1979.
6. Jhaveri R, Rosenfeld W, Salazar JD, et al: High titer multiple dose therapy with HBIG in newborn infants of HBsAg positive mothers. J Pediatr 97(2):305–8, 1980.
7. Hoofnagle JH, Seeff LB, Bales ZB, et al: Passive-active immunity from hepatitis B immune globulin. Ann Intern Med 91(6):813-8, 1979.
8. Scheiermann N, Kuwert EK: Uptake and elimination of hepatitis B immunoglobulins after intramuscular application in man. Dev Biol Stand 54:347-55, 1983.
9. Recommendations of the Immunization Practices Advisory Committee (ACIP): Hepatitis B Virus: A Comprehensive Strategy for Eliminating Transmission in the United States Through Universal Childhood Vaccination. Appendix A: Postexposure Prophylaxis for Hepatitis B. MMWR 40(RR-13):21-25, 1991.
10. Stevens CE, Beasley RP, Tsui J, et al: Vertical transmission of hepatitis B antigen in Taiwan. N Engl J Med 292(15):771-4, 1975.
11. Shiraki K, Yoshihara N, Kawana T, et al: Hepatitis B surface antigen and chronic hepatitis in infants born to asymptomatic carrier mothers. Am J Dis Child 131(6):644-7, 1977.
12. Recommendation of the Immunization Practices Advisory Committee (ACIP): Immune globulins for protection against viral hepatitis. MMWR 30(34):423-8; 433-5, 1981.
13. Okada K, Kamiyama I, Inomata M, et al: e antigen and anti-e in the serum of asymptomatic carrier mothers as indicators of positive and negative transmission of hepatitis B virus to their infants. N Engl J Med 294(14):746-9, 1976.
14. Beasley RP, Trepo C, Stevens CE, et al: The e antigen and vertical transmission of hepatitis B surface antigen. Am J Epidemiol 105(2):94-8, 1977.
15. Beasley RP, Hwang LY, Lee GCY, et al: Prevention of perinatally transmitted hepatitis B virus infections with hepatitis B immune globulin and hepatitis B vaccine. Lancet 2(8359): 1099-102, 1983.
16. Recommendation of the Immunization Practices Advisory Committee (ACIP): Recommendations for protection against viral hepatitis. MMWR 34(22):313–35, 1985.
17. Szmuness W, Stevens CE, Olesko WR, et al: Passive-active immunisation against hepatitis B: immunogenicity studies in adult Americans. Lancet 1:575–77, 1981.
18. Recommendations of the Advisory Committee on Immunization Practices (ACIP) and the AmericanAcademy of Family Physicians (AAFP): General recommendations on immunization. MMWR 2002:51 (RR02), 1-36.
19. Beasley RP, Hwang LY: Measles vaccination not interfered with by hepatitis B immune globulin. Lancet 1:161, 1982.
20. Ellis EF, Henney CS: Adverse reactions following administration of human gamma globulin. J Allerg 43(1):45-54, 1969.
21. Recommendations of the Immunization Practices Advisory Committee (ACIP): Update on Adult Immunization. Table 9. Recommendations for postexposure prophylaxis for percutaneous or permucosal exposure to hepatitis B, United States. MMWR 40(RR-12):70, 1991.
22. Recommendations of the Immunization Practices Advisory Committee (ACIP): Update on Adult Immunization. Table 10. Recommendations for postexposure prophylaxis for perinatal and sexual exposure to hepatitis B, United States. MMWR 40(RR-12):71, 1991.

Rev. 8/2022

Grifols Therapeutics LLC
Research Triangle Park, NC 27709 USA
U.S. License No. 1871

3063868

PACKAGE LABEL

≥ 110 IU / 0.5 mL
Hepatitis B
Immune
Globulin
(Human)
HyperHEP B®
0.5 mL
Solution for Intramuscular
Injection
≥ 220 IU/mL
Contents: One 0.5 mL neonatal
single-dose disposable syringe
with attached needle.
Hepatitis B Immune Globulin
(Human) is a sterile solution
of immunoglobulin containing
15% — 18% protein stabilized
with 0.16 M to 0.26 M glycine.
FOR INTRAMUSCULAR
INJECTION ONLY.
DO NOT GIVE INTRAVENOUSLY.
NDC 13533-636-03
GRIFOLS
The patient and physician should
discuss the risks and benefits of this
product.
The potency of the solution in each
syringe is equivalent to or exceeds
that of the U.S. Food and Drug
Administration Reference Hepatitis B
Immune Globulin. The U.S. reference
has been tested against the World
Health Organization standard
Hepatitis B Immune Globulin and
found to be equal to 220 international
units (IU) per mL.
0.5 mL
For complete dosage and
administration information, read
enclosed package insert.
For directions for syringe usage, see
enclosed package insert.
Store at 2°C to 8°C (36°F to 46°F).
Do not freeze.
Do not use if the syringe is prematurely
engaged.
Not returnable for credit or
exchange.
Rx only
Not made with natural rubber latex.
No preservative
Discard unused portion.
Grifols Therapeutics LLC
Research Triangle Park,
NC 27709 USA
U.S. License No. 1871
GRIFOLS
NDC 13533-636-03 GTIN 00313533636036
LOT XXXXXXXXXXXX
EXP DDMMMYYYY
SN XXXXXXXXXXXXXXXXXX
HyperHEP B®
≥ 110 IU / 0.5 mL
Carton: 3060176

3060171
Lot
Exp.
Hepatitis B Immune
Globulin (Human)
HyperHEP B® ≥ 110 IU/0.5 mL
Contents: One 0.5 mL
Neonatal Single Dose
The patient and physician should discuss
the risks and benefits of this product.
Grifols Therapeutics LLC
RTP, NC 27709 USA
U.S. License No. 1871

≥ 220 IU / 1 mL
Hepatitis B
Immune
Globulin
(Human)
HyperHEP B®
1 mL
Solution for Intramuscular
Injection
≥ 220 IU/mL
FOR INTRAMUSCULAR
INJECTION ONLY. DO NOT GIVE
INTRAVENOUSLY.
NDC 13533-636-01
GRIFOLS
The patient and physician should
discuss the risks and benefits of
this product.
One Single-Dose Vial
Discard unused portion.
For complete dosage and
administration information, read
enclosed package insert.
Store at 2°C to 8°C (36°F to
46°F). Do not freeze.
1 mL
If the shrink band is absent or
shows any sign of tampering, do
not use the product and notify
Grifols Therapeutics LLC
immediately.
Not returnable for credit or
exchange.
Rx only
GRIFOLS
Hepatitis B Immune Globulin
(Human) is a sterile solution of
immunoglobulin containing 15%–18% protein
stabilized with 0.16 M to 0.26 M glycine.
1 mL
Grifols Therapeutics LLC
Research Triangle Park,
NC 27709 USA
U.S. License No. 1871
GRIFOLS
The potency is equivalent to or
exceeds that of the U.S. Food and
Drug Administration Reference
Hepatitis B Immune Globulin. The
U.S. reference has been tested
against the World Health
Organization standard Hepatitis B
Immune Globulin and found to be
equal to 220 international units
(IU) per mL.
1 mL
Not made with natural rubber
latex.
No preservative
GRIFOLS
NDC 13533-636-01
GTIN 00313533636012
LOT XXXXXXXXXX
EXP DDMMMYYYY
SN XXXXXXXXXXXXXXXX
HyperHEP B®
≥ 220 IU / 1 mL
Carton: 3060178

NDC 13533-636-10 ≥ 220 IU / 1 mL
Hepatitis B Immune
Globulin (Human)
HyperHEP B® ≥ 220 IU/mL
The patient and physician should discuss the risks and
benefits of this product. Dosage & Administration: See insert.
Grifols Therapeutics LLC
RTP, NC 27709 USA U.S. License No. 1871
3060173
Lot / Exp.